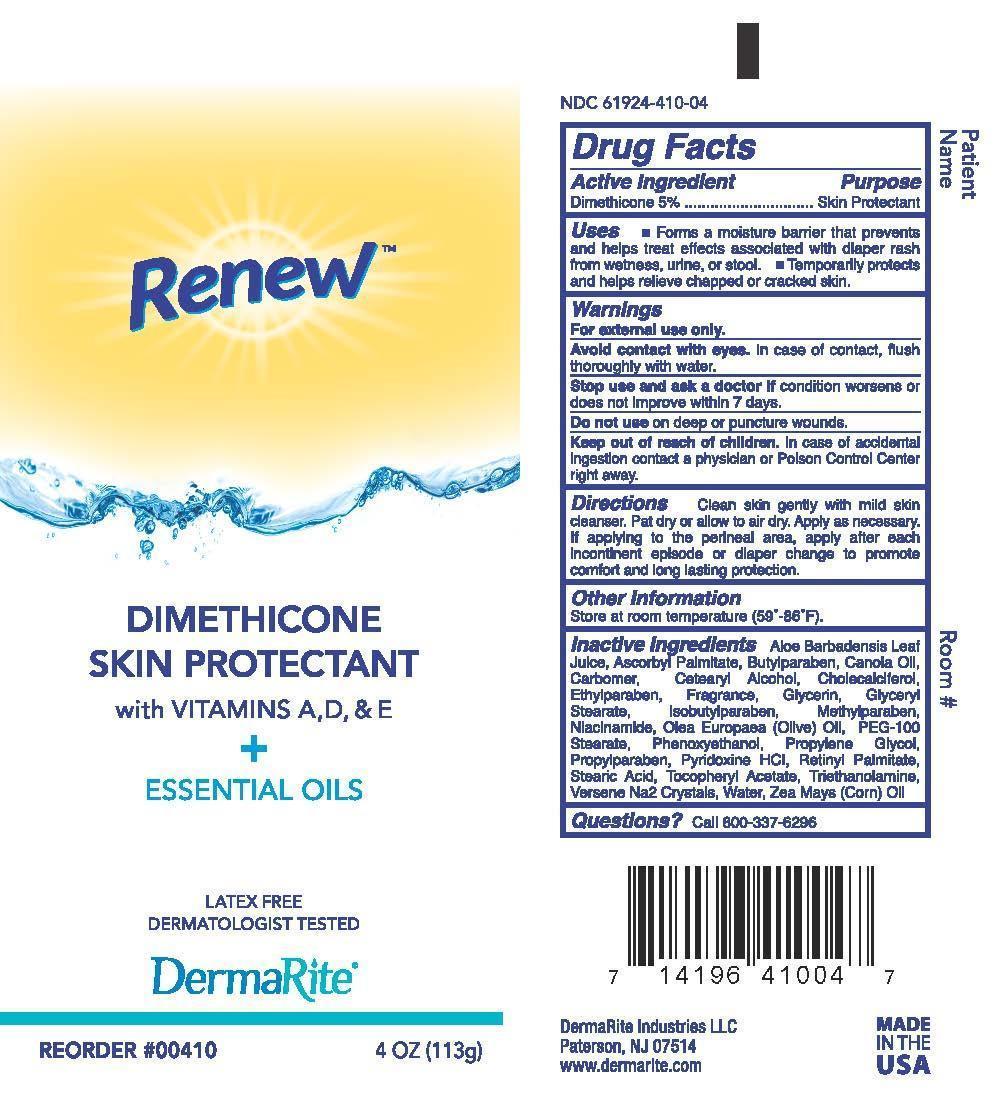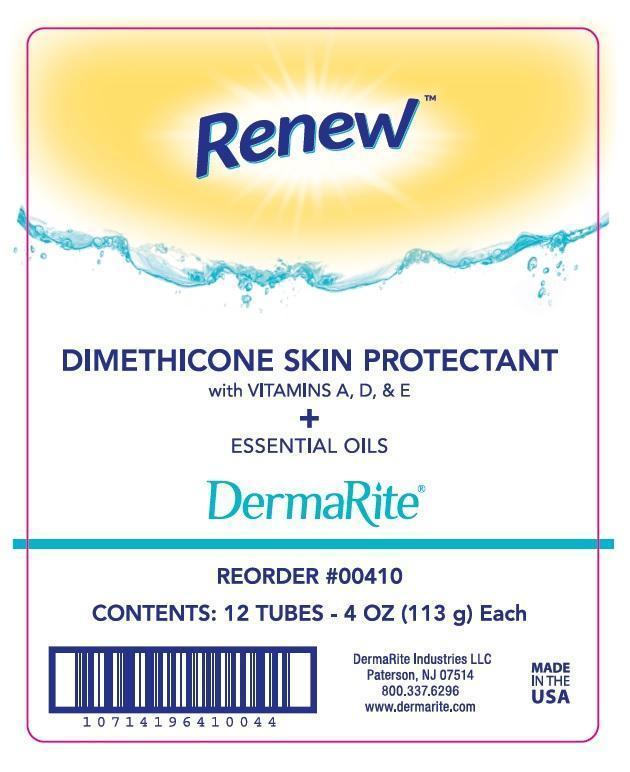 DRUG LABEL: Renew Dimethicone Skin Protectant
NDC: 61924-410 | Form: CREAM
Manufacturer: Dermarite Industries LLC
Category: otc | Type: HUMAN OTC DRUG LABEL
Date: 20241205

ACTIVE INGREDIENTS: DIMETHICONE 0.05 g/100 g
INACTIVE INGREDIENTS: ALOE VERA LEAF; ASCORBYL PALMITATE; BUTYLPARABEN; CANOLA OIL; CARBOMER 940; CETOSTEARYL ALCOHOL; CHOLECALCIFEROL; ETHYLPARABEN; GLYCERIN; GLYCERYL MONOSTEARATE; ISOBUTYLPARABEN; METHYLPARABEN; NIACINAMIDE; OLIVE OIL; PEG-100 STEARATE; PHENOXYETHANOL; PROPYLENE GLYCOL; PROPYLPARABEN; PYRIDOXINE HYDROCHLORIDE; VITAMIN A PALMITATE; STEARIC ACID; .ALPHA.-TOCOPHEROL ACETATE; TROLAMINE; EDETATE DISODIUM; WATER; CORN OIL

DRUG LISTING: Renew Dimethicone Skin Protectant

Active Ingredient:

Dimethicone 5%

Purpose:

Skin Protectant

Uses:

- Forms a moisture barrier that prevents and helps treat effects associated with diaper rash from wetness, urine, or stool.
- Temporarily protects and helps relieve chapped or cracked skin.

Warnings:

- For external use only.
- Avoid contact with eyes. In case of contact, flush thoroughly with water.
- Stop use and ask a doctor if condition worsens or does not improve within 7 days.
- Do not use on deep or punctured wounds.

Warnings:

Keep out of reach of children. In case of accidental ingestion contact physician or Poison Control Center right away.

Directions:

Clean skin gently with mild skin cleanser. Pat dry or allow to air dry. Apply as necessary. If applying to perineal area, apply after each incontinent episode or diaper change to promote comfort and long lasting protection.

Other Information:

Store at room temperature (59o- 86oF)

Inactive Ingredients:

Aloe Barbadensis Leaf Juice, Aluminum Stearate, Cera Alba, Cholecalciferol, Chloroxylenol, Corn Oil, Imidiazolidinyl Urea, Dicocoyl Pentaerythrityl Distearyl Citrate, Fragrance, Lanolin, Methylparaben, Mineral Oil, Paraffin wax, Petrolatum, Phenoxyethanol, Propylene Glycol, Propylparaben, Retinyl Palmitate, Sorbitan Sesquioleate, Tocopheryl Acetate, Water.

Questions?

Call 1-800-37-6296